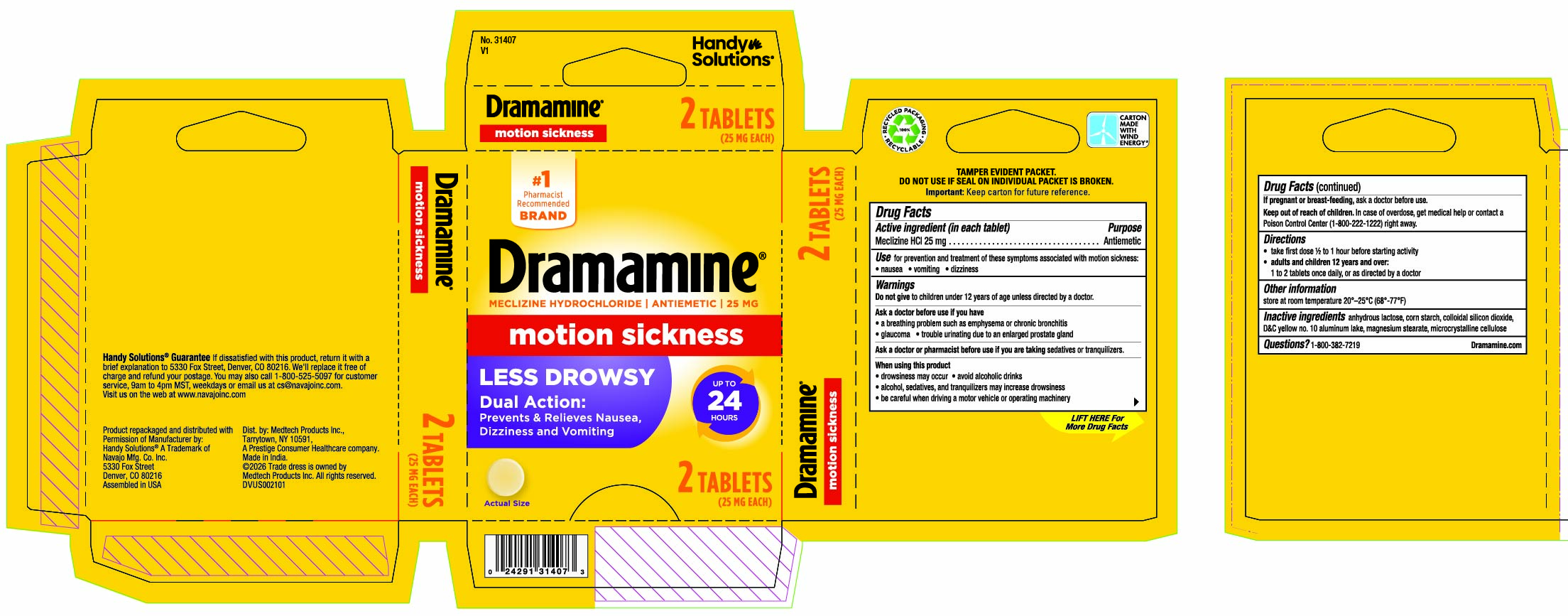 DRUG LABEL: Dramamine Less Drowsy
NDC: 67751-242 | Form: TABLET
Manufacturer: Navajo Manufacturing Company Inc.
Category: otc | Type: HUMAN OTC DRUG LABEL
Date: 20260218

ACTIVE INGREDIENTS: MECLIZINE HYDROCHLORIDE 25 mg/1 1
INACTIVE INGREDIENTS: ANHYDROUS LACTOSE; STARCH, CORN; SILICON DIOXIDE; D&C YELLOW NO. 10; MAGNESIUM STEARATE; CELLULOSE, MICROCRYSTALLINE

Dramamine Less Drowsy

Drug Facts

Active ingredient

(in each tablet)

Meclizine HCI 25 mg

Purpose

Antiemetic

Use

for prevention and treatment of these symptoms associated with motion sickness:

- nausea
- vomiting
- dizziness

Warnings

Do notgive

to children under 12 years of age unless directed by a doctor.

Ask a doctor before use if you have

- a breathing problem such as emphysema or chronic bronchitis
- glaucoma
- trouble urinating due to an enlarged prostate gland

Ask a doctor or pharmacist before use if you aretaking

sedatives or tranquilizers.

When using this product

- drowsiness may occur
- avoid alcoholic drinks
- alcohol, sedatives, and tranquilizers may increase drowsiness
- be careful when driving a motor vehicle or operating machinery

If pregnant or breast-feeding,

ask a doctor before use.

Keep out of reach of children.

In case of overdose, get medical help or contact a Poison Control Center (1-800-222-1222) right away.

Directions

- take first dose 1/2 to 1 hour before starting activity
- adults and children 12 years and over:1 to 2 tablets once daily, or as directed by a doctor

Other information

- store at room temperature 20 - 25ºC (68 - 77ºF)

Inactive ingredients

anhydrous lactose, corn starch, colloidal silicon dioxide, D&C yellow no. 10 aluminum lake, magnesium stearate, microcrystalline cellulose

Questions?

1-800-382-7219

Dramamine.com